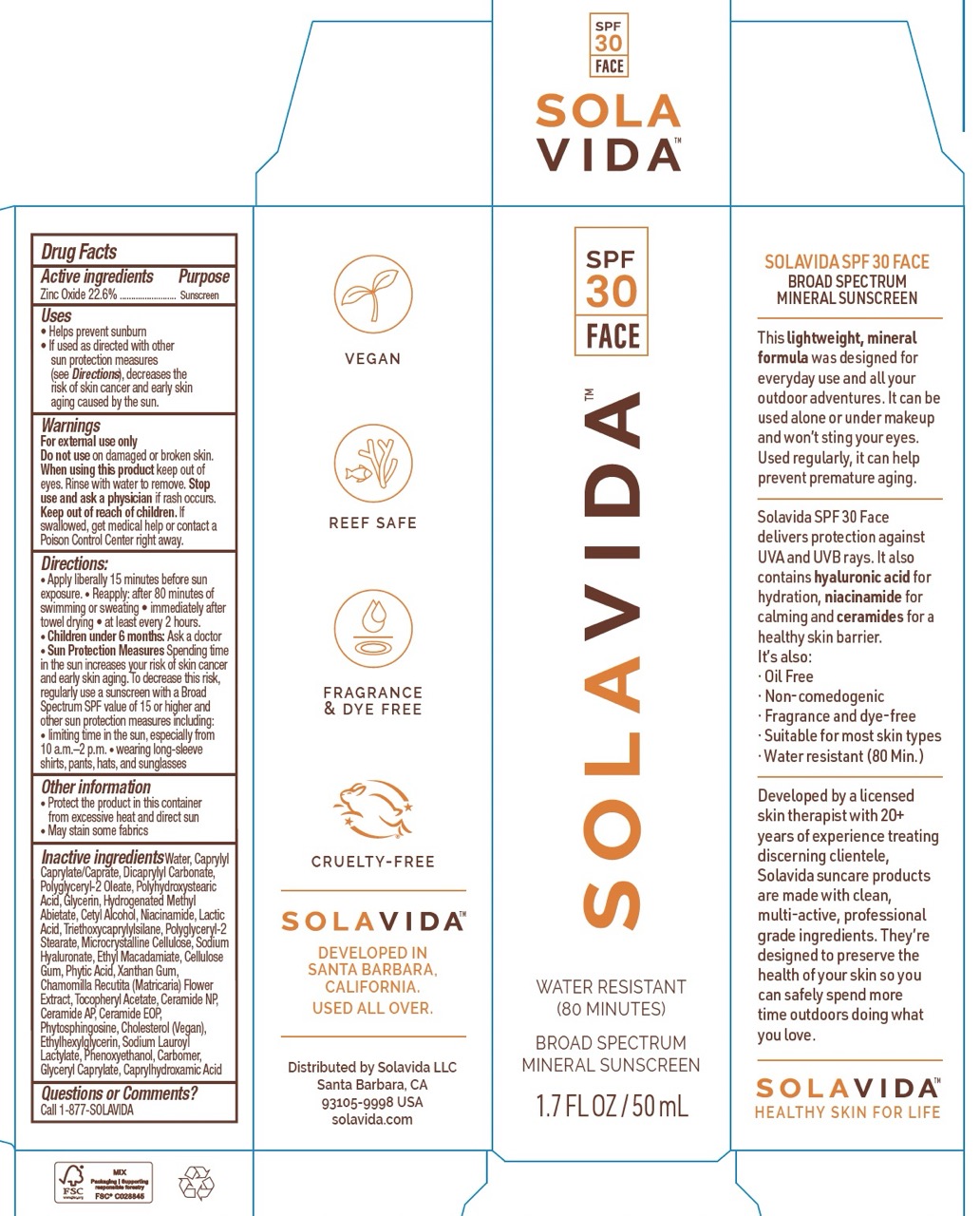 DRUG LABEL: Solavida Broad Spectrum Mineral Sunscreen SPF 30 - Face
NDC: 87422-001 | Form: LOTION
Manufacturer: Solavida, LLC
Category: otc | Type: HUMAN OTC DRUG LABEL
Date: 20260209

ACTIVE INGREDIENTS: ZINC OXIDE 22.6 g/100 mL
INACTIVE INGREDIENTS: WATER; ALPHA-TOCOPHEROL ACETATE; PHYTOSPHINGOSINE; CERAMIDE AP; CAPRYLYL CAPRYLATE/CAPRATE; HYDROGENATED METHYL ABIETATE; TRIETHOXYCAPRYLYLSILANE; CERAMIDE 1; GLYCERIN; CAPRYLHYDROXAMIC ACID; MICROCRYSTALLINE CELLULOSE; PHENOXYETHANOL; DICAPRYLYL CARBONATE; POLYGLYCERYL-2 OLEATE; XANTHAN GUM; SODIUM LAUROYL LACTYLATE; NIACINAMIDE; SODIUM HYALURONATE; ETHYLHEXYLGLYCERIN; GLYCERYL CAPRYLATE; POLYGLYCERYL-2 STEARATE; CELLULOSE GUM; ETHYL MACADAMIATE; CARBOMER; MATRICARIA CHAMOMILLA FLOWERING TOP; CHOLESTEROL; POLYHYDROXYSTEARIC ACID (2300 MW); PHYTIC ACID; LACTIC ACID; CERAMIDE NP; CETYL ALCOHOL

Solavida Mineral Sunscreen SPF 30 Face - 1.7 fl oz / 50 ml

Active Ingredient

Zinc Oxide 22.6

Purpose

Sunscreen

Uses

- helps prevent sunburn

- if used as directed with other sun protection measures (see Directions), decreases the risk of skin cancer and early skin aging caused by the sun.

Warnings

For external use only.

Do not use

on damaged or broken skin.

When using this product

keep out of eyes. Rinse with water to remove.

Stop use and ask a physician if

rash occurs.

Keep out of reach of children

If swallowed, get medical help or contact a Poison Control Center right away.

Directions

- Apply liberally 15 minutes before sun exposure.

- Reapply: after 80 minutes of swimming or sweating • immediately after towel drying • at least every 2 hours

- Children under 6 months: Ask a doctor

- Sun Protection Measures: Spending time in the sun increases your risk of skin cancer and early skin aging. To decrease this risk, regularly use a sunscreen with a Broad Spectrum SPF value of 15 or higher and other sun protection measures including: • limiting time in the sun, especially from 10 a.m. - 2 p.m. • wearing long sleeve shirts, pants, hats, and sunglasses.

Other information

- Protect the product in this container from excessive heat and direct sun

- May stain some fabrics

Inactive ingredients

Water (Aqua), Caprylyl Caprylate/Caprate, Dicaprylyl Carbonate, Polyglyceryl-2 Oleate, Polyhydroxystearic Acid, Glycerin, Hydrogenated Methyl Abietate, Cetyl Alcohol, Niacinamide, Lactic Acid, Triethoxycaprylylsilane, Polyglyceryl-2 Stearate, Microcrystalline Cellulose, Sodium Hyaluronate, Ethyl Macadamiate, Cellulose Gum, Phytic Acid, Xanthan Gum, Chamomilla Recutita (Matricaria) Flower Extract*, Tocopheryl Acetate, Ceramide NP, Ceramide AP, Ceramide EOP, Phytosphingosine, Cholesterol (Vegan), Ethylhexylglycerin, Sodium Lauroyl Lactylate, Phenoxyethanol, Carbomer, Glyceryl Caprylate, Caprylhydroxamic Acid.

Questions or Comments?

Call 1-877-SOLAVIDA

Principal Display Panel

SPF
30
FACE

SOLAVIDA™

WATER RESISTANT
(80 MINUTES)

BROAD SPECTRUM
MINERAL SUNSCREEN

1.75 FL OZ / 50 ML